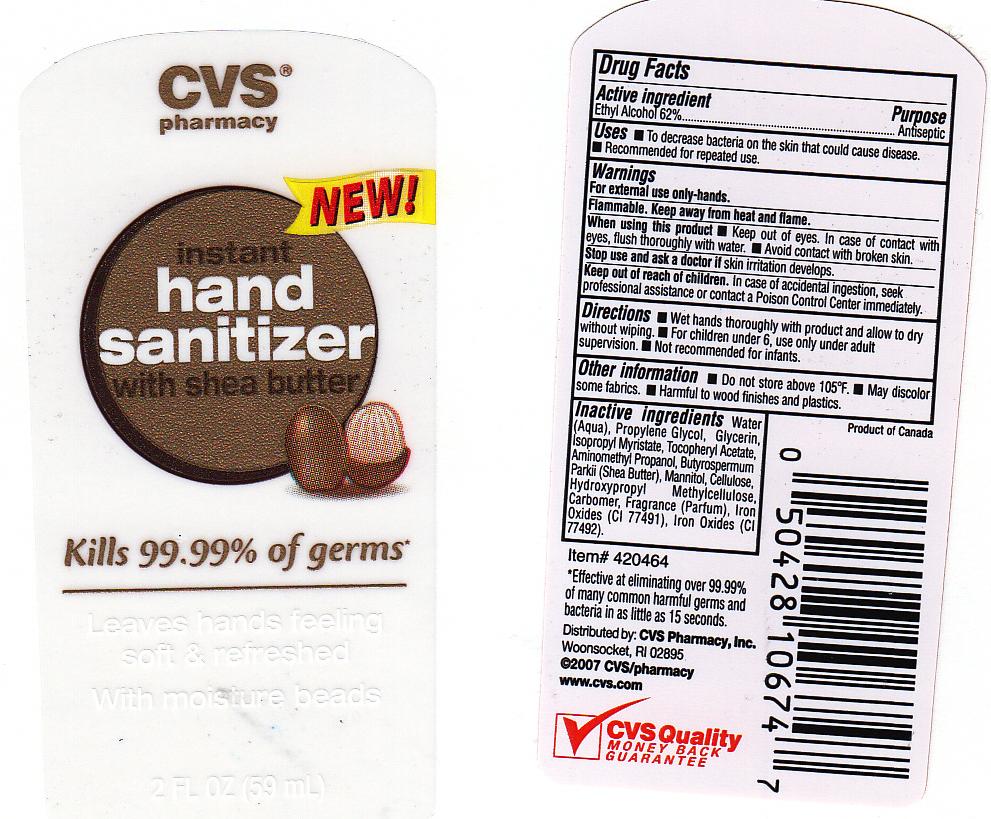 DRUG LABEL: INSTANT HAND SANITIZER
NDC: 59779-224 | Form: GEL
Manufacturer: CVS PHARMACY
Category: otc | Type: HUMAN OTC DRUG LABEL
Date: 20110131

ACTIVE INGREDIENTS: ALCOHOL 62 mL/100 mL
INACTIVE INGREDIENTS: WATER; PROPYLENE GLYCOL; GLYCERIN; ISOPROPYL MYRISTATE; .ALPHA.-TOCOPHEROL ACETATE, D-; AMINOMETHYLPROPANOL; SHEA BUTTER; MANNITOL; POWDERED CELLULOSE; HYPROMELLOSES; CARBOMER 934; FERRIC OXIDE RED; FERRIC OXIDE YELLOW

DRUG FACTS

ACTIVE INGREDIENT

ETHYL ALCOHOL 62%

PURPOSE

ANTISEPTIC

USES

TO DECREASE BACTERIA ON THE SKIN THAT COULD CAUSE DISEASE. RECOMMENDED FOR REPEATED USE.

WARNINGS

FOR EXTERNAL USE ONLY-HANDS.

FLAMMABLE. KEEP AWAY FROM HEAT AND FLAME.

WHEN USING THIS PRODUCT

KEEP OUT OF EYES. IN CASE OF CONTACT WITH EYES, FLUSH THOROUGHLY WITH WATER. AVOID CONTACT WITH BROKEN SKIN.

STOP USE AND ASK A DOCTOR

IF SKIN IRRITATION DEVELOPS.

KEEP OUT OF REACH OF CHILDREN

IN CASE OF ACCIDENTAL INGESTION, SEEK PROFESSIONAL ASSISTANCE OR CONTACT A POISON CONTROL CENTER IMMEDIATELY.

DIRECTIONS

WET HANDS THOROUGHLY WITH PRODUCT AND ALLOW TO DRY WITHOUT WIPING. FOR CHILDREN UNDER 6, USE ONLY UNDER ADULT SUPERVISION. NOT RECOMMENDED FOR INFANTS.

OTHER INFORMATION

DO NOT STORE ABOVE 105 DEGREES FAHRENHEIT. MAY DISCOLOR SOME FABRICS, HARMFUL TO WOOD FINISHES AND PLASTICS.

INACTIVE INGREDIENTS

WATER, PROPYLENE GLYCOL, GLYCERIN, ISOPROPYL MYRISTATE, TOCOPHERYL ACETATE, AMINOMETHYL PROPANOL, BUTYROSPERMUM PARKII (SHEA BUTTER), MANNITOL, CELLULOSE, HYDROXYPROPYL METHYLCELLULOSE, CARBOMER, FRAGRANCE, IRON OXIDES (CI 77491), IRON OXIDES (CI 77492).